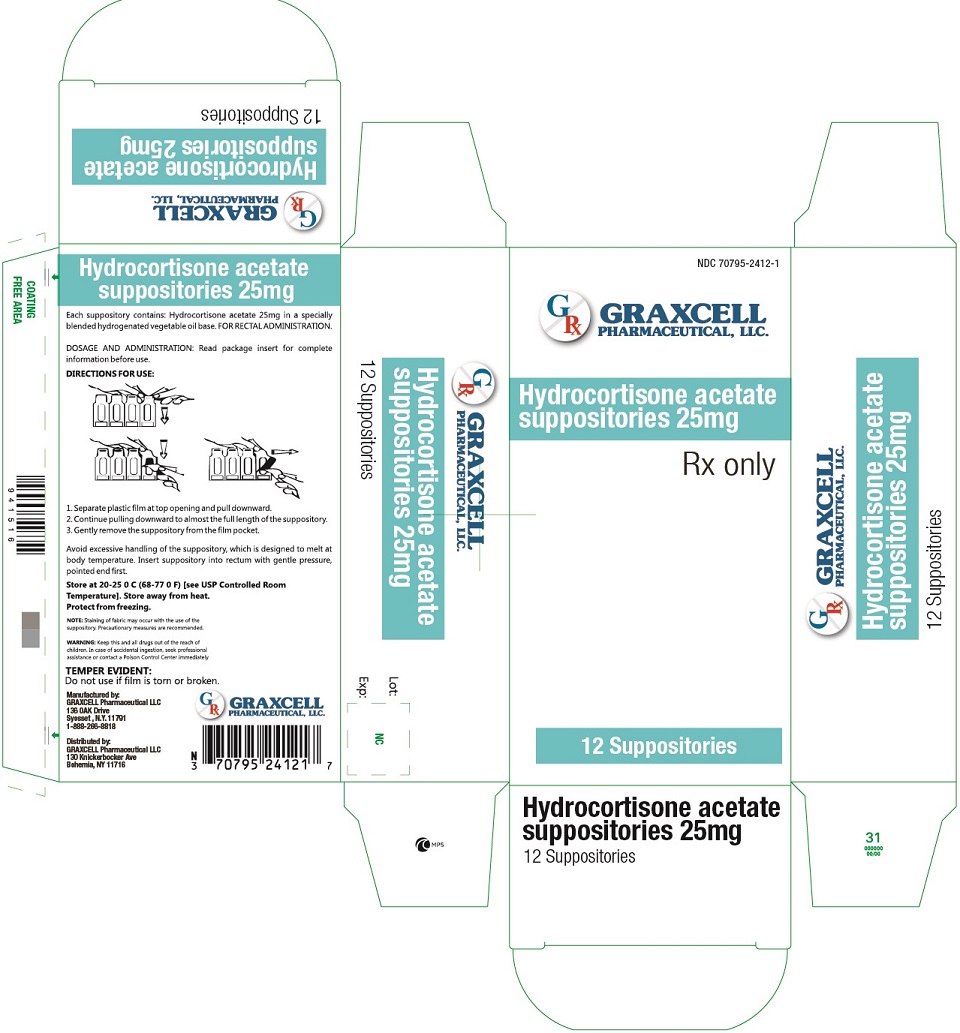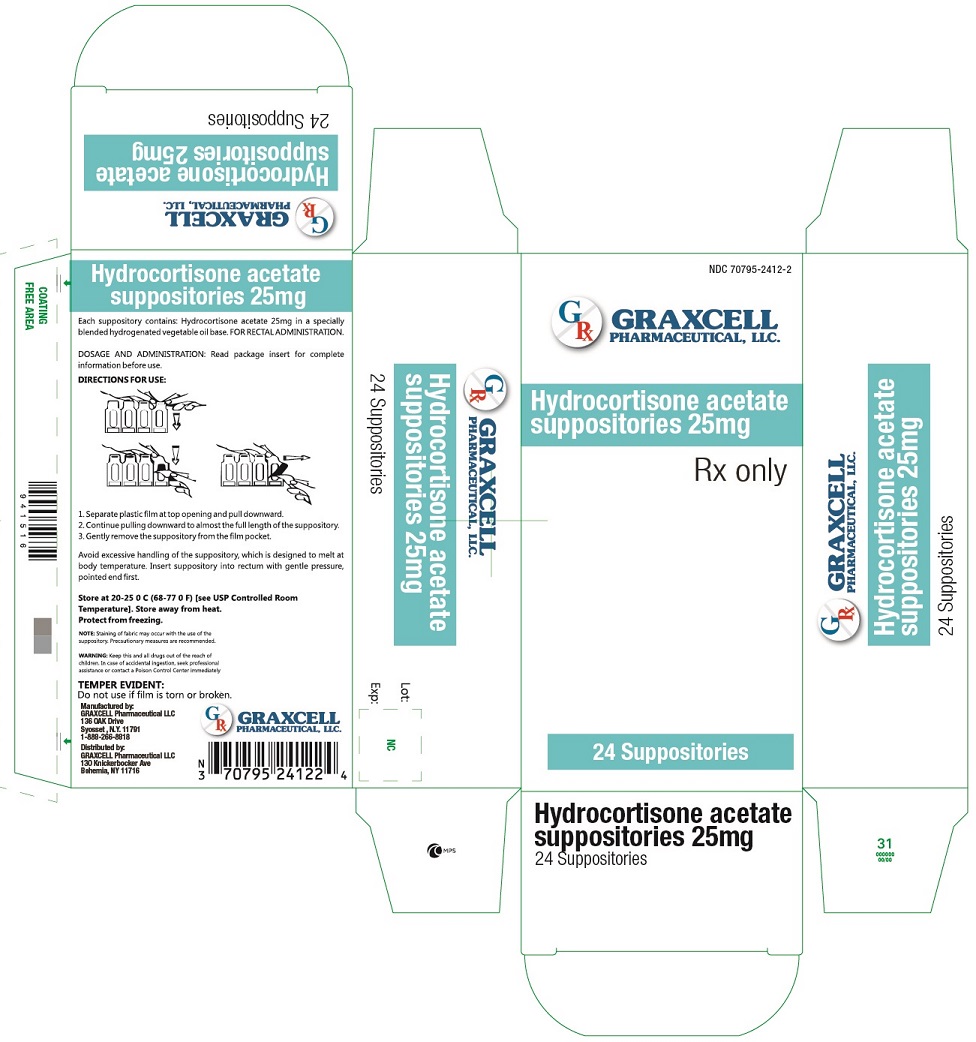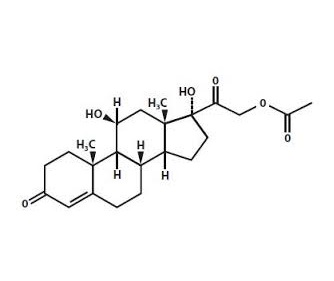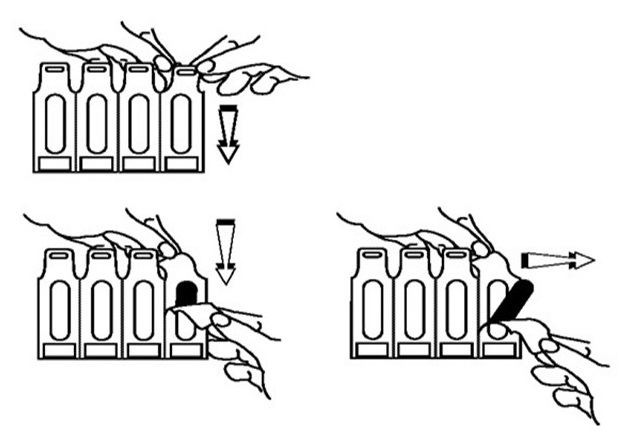 DRUG LABEL: HYDROCORTISONE ACETATE
NDC: 70795-2412 | Form: SUPPOSITORY
Manufacturer: GRAXCELL PHARMACEUTICAL, LLC.
Category: prescription | Type: HUMAN PRESCRIPTION DRUG LABEL
Date: 20211221

ACTIVE INGREDIENTS: HYDROCORTISONE ACETATE 25 mg/1 1
INACTIVE INGREDIENTS: HYDROGENATED COCO-GLYCERIDES

HYDROCORTISONE ACETATE SUPPOSITORY 25MG, 70795-2412

Graxcell Pharmaceutical, llc. Disclaimer: This drug has not been found by FDA to be safe and effective, and this labelling has not been approved by FDA. Hydrocortisone acetae, 25mg. Rectal suppositories.

Hydrocortisone Acetate is a corticosteroid designated chemically as pregn-4-ene-3, 20-dione, 21-(acetyloxy)-11, 17-dihydroxy-(11β) with the following structural formula:

Each rectal suppository contains hydrocortisone acetate, USP 25 mg in a specially blended hydrogenated vegetable oil base

CLINICAL PHARMACOLOGY

In normal subjects, about 26% of hydrocortisone acetate is absorbed when the suppository is applied to the rectum. Absorption of hydrocortisone acetate may vary across abraded or inflamed surfaces. Topical steroids are primarily effective because of their anti-inflammatory, anti-pruritic and vasconstrictive action.

INDICATIONS AND USAGE

Hydrocortisone acetate suppositories are indicated for the use in inflamed hemorrhoids, post-irradiation (factitial) proctitis; as an adjunct in the treatment of chronic ulcerative colitis; cryptitis; and other inflammatory conditions of anorectum and puritus ani.

CONTRAINDICATIONS

Hydrocortisone Acetate suppositories are contraindicated in those patients having a history of hypersensitivity to hydrocortisone acetate or any of the components

Do not use unless adequate proctologic examination is made. If irritation develops, the product should be discontinued and appropriate therapy instituted. In the presence of an infection, the use of an appropriate antifungal or antibacterial agent should be instituted. If a favorable response does not occur promptly, the corticosteroid should be discontinued until the infection has been adequately controlled.

Carcinogenic: No long-term studies in animals have been performed to evaluate the carcinogenic potential of corticosteroid suppositories.

ADVERSE REACTIONS

The following local adverse reactions have been reported with hydrocortisone acetate suppositories; burning, itching, irritation, dryness, folliculitis, hypopigmentation, allergic contact dermatitis, secondary infection.

To report suspected adverse reactions, contact

Graxcell pharmaceutical, llc.

1-888-266-8818 or

FDA @ 1-800-FDA-1088 or

www.fda.gov/medwatch

OVERDOSAGE

If signs and symptoms of systemic overdosage occur, discontinue use.

DOSAGE AND ADMINISTRATION

Usual Dosage: One suppository in the rectum morning and night for two weeks, in nonspecific proctitis. In more severe cases, one suppository three times daily: or two suppositories twice daily. In factitial proctitis, recommended therapy in six to eight weeks or less, according to the response of the individual case.

Rx only.

OPENING INSTRUCTIONS

Avoid excessive handling of the suppository. It is designed to melt at body temperature.

1. Separate plastic film at top opening and pull downward.

2. Continue pulling downward to almost the full length of the suppository.

3. Gently remove the suppsitory from the film pocket.

HOW SUPPLIED

Hydrocortisone Acetate suppositories 25mg are white,cyclinder shaped, with one end tapered.

Package of 12 NDC 70795-2412-1

and

Package of 24 NDC 70795-2412-2

STORAGE AND HANDLING

Store at 20º-25ºC (68º-77ºF) [See USP Controlled Room Temperature]. Store away from heat. Protect from freezing.

Manufactured for:

Graxcell pharmaceutical, LLC.

130 knickerbocker ave,Bohemia, NY 11716

Manufactured by:

Graxcell pharmaceutical, llc.

136 OAk Drive,

syosset, NY 11791

1-888-266-8818.

DRUG ABUSE AND DEPENDENCE

Drug abuse and dependece have not been reported in patients treated with Hydrocortisone acetate suppositories.